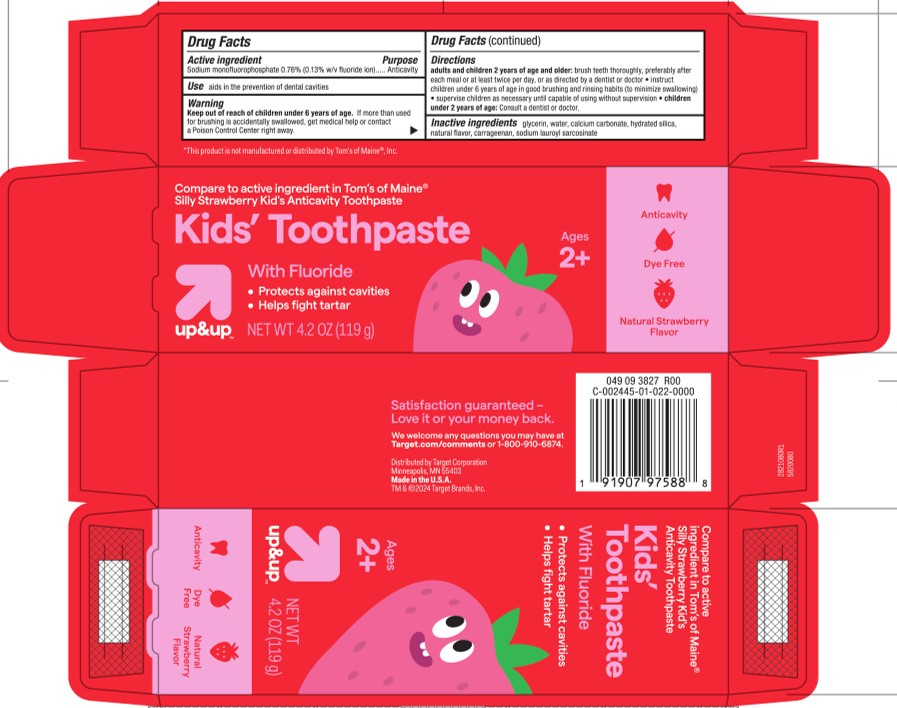 DRUG LABEL: Kids Strawberry FTP
NDC: 11673-441 | Form: PASTE, DENTIFRICE
Manufacturer: Target
Category: otc | Type: HUMAN OTC DRUG LABEL
Date: 20251113

ACTIVE INGREDIENTS: SODIUM MONOFLUOROPHOSPHATE 0.13 g/100 g
INACTIVE INGREDIENTS: WATER; CALCIUM CARBONATE; HYDRATED SILICA; CARRAGEENAN; GLYCERIN; SODIUM LAUROYL SARCOSINATE

5820080 Target Kids Strawberry Fluoride Toothpaste (8015276)

ACTIVE INGREDIENT

Sodium Monofluorophosphate 0.76% (0.13% w/v) ..... Anticavity

INACTIVE INGREDIENT

glycerin, water, calcium carbonate, hydrated silica, natural flavor, carrageenan, sodium lauroyl sarcosinate

DOSAGE AND ADMINISTRATION

Adults and children 2 years of age and older: Brush teeth thoroughly, preferably after each meal or at least twice a day, or as directed by a dentist or doctor. Instruct children under 6 years of age in good brushing and rinsing habits (to minimize swallowing). Supervise children as necessary until capable of using wihtout supervision.
Children under 2 years of age: Consult a dentist or doctor.

Keep out of reach of children under 6 years old. If more than used for brushing is accidentally swallowed, get medical help or call a Posion control center rigth away.

Keep out of reach of children under 6 years old. If more than used for brushing is accidentally swallowed, get medical help or call a Posion control center rigth away.

PURPOSE

Aids in the prevention of dental cavities.

INDICATIONS AND USAGE

Adults and children 2 years of age and older: Brush teeth thoroughly, preferably after each meal or at least twice a day, or as directed by a dentist or doctor. Instruct children under 6 years of age in good brushing and rinsing habits (to minimize swallowing). Supervise children as necessary until capable of using wihtout supervision.
Children under 2 years of age: Consult a dentist or doctor.